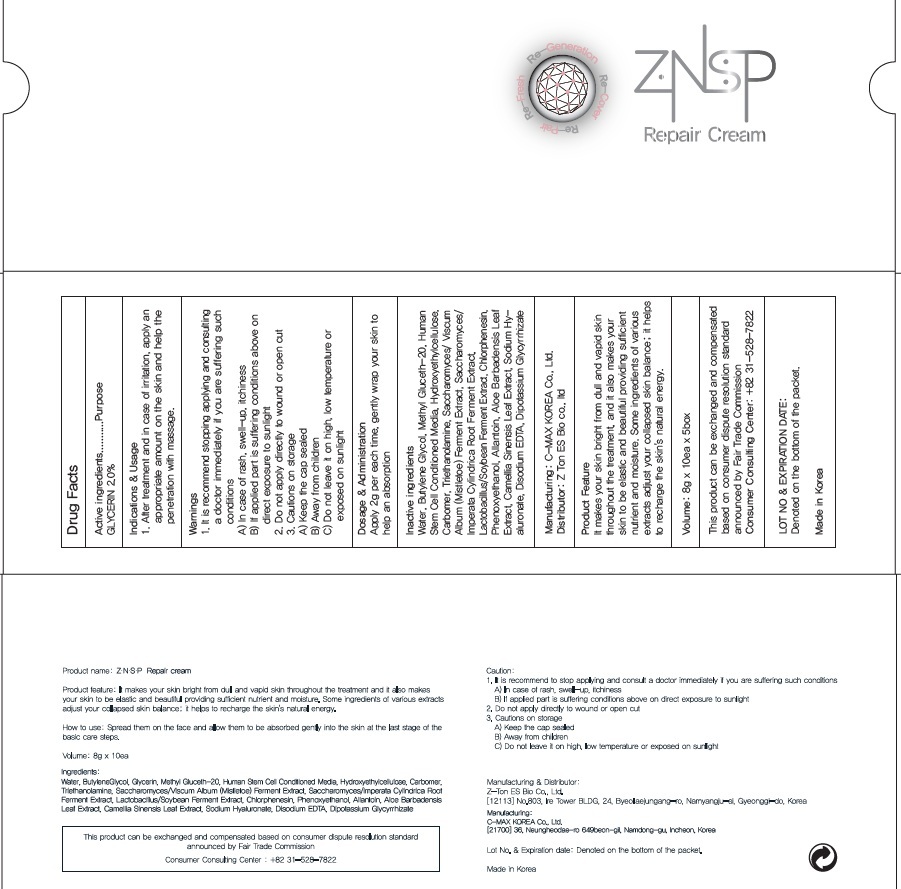 DRUG LABEL: ZNSP Repair
NDC: 70749-020 | Form: CREAM
Manufacturer: Z-TON ES BIO CO., LTD.
Category: otc | Type: HUMAN OTC DRUG LABEL
Date: 20160602

ACTIVE INGREDIENTS: GLYCERIN 0.16 g/8 g
INACTIVE INGREDIENTS: Water; Butylene Glycol

ACTIVE INGREDIENT

Active Ingredient: GLYCERIN 2.0%

INACTIVE INGREDIENT

Inactive Ingredients: Water, Butylene Glycol, Methyl Gluceth-20, Human Stem Cell Conditioned Media, Hydroxyethylcellulose, Carbomer, Triethanolamine, Saccharomyces/Viscum Album (Mistletoe) Ferment Extract, Saccharomyces/Imperata Cylindrica Root Ferment Extract, Lactobacillus/Soybean Ferment Extract, Chlorphenesin, Phenoxyethanol, Allantoin, Aloe Barbadensis Leaf Extract, Camellia Sinensis Leaf Extract, Sodium Hyaluronate, Disodium EDTA, Dipotassium Glycyrrhizate

PURPOSE

Purpose: Skin Protectant

WARNINGS

Warnings: 1. It is recommend stopping applying and consulting a doctor immediately if you are suffering such conditions A) In case of rash, swell-up, itchiness B) If applied part is suffering conditions above on direct exposure to sunlight 2. Do not apply directly to wound or open cut 3. Cautions on storage A) Keep the cap sealed B) Away from children C) Do not leave it on high, low temperature or exposed on sunlight

KEEP OUT OF REACH OF CHILDREN

INDICATIONS & USAGE

1. After treatment and in case of irritation, apply an appropriate amount on the skin and help the penetration with massage.

DOSAGE & ADMINISTRATION

Apply 2ml per each time, gently wrap your skin to help an absorption